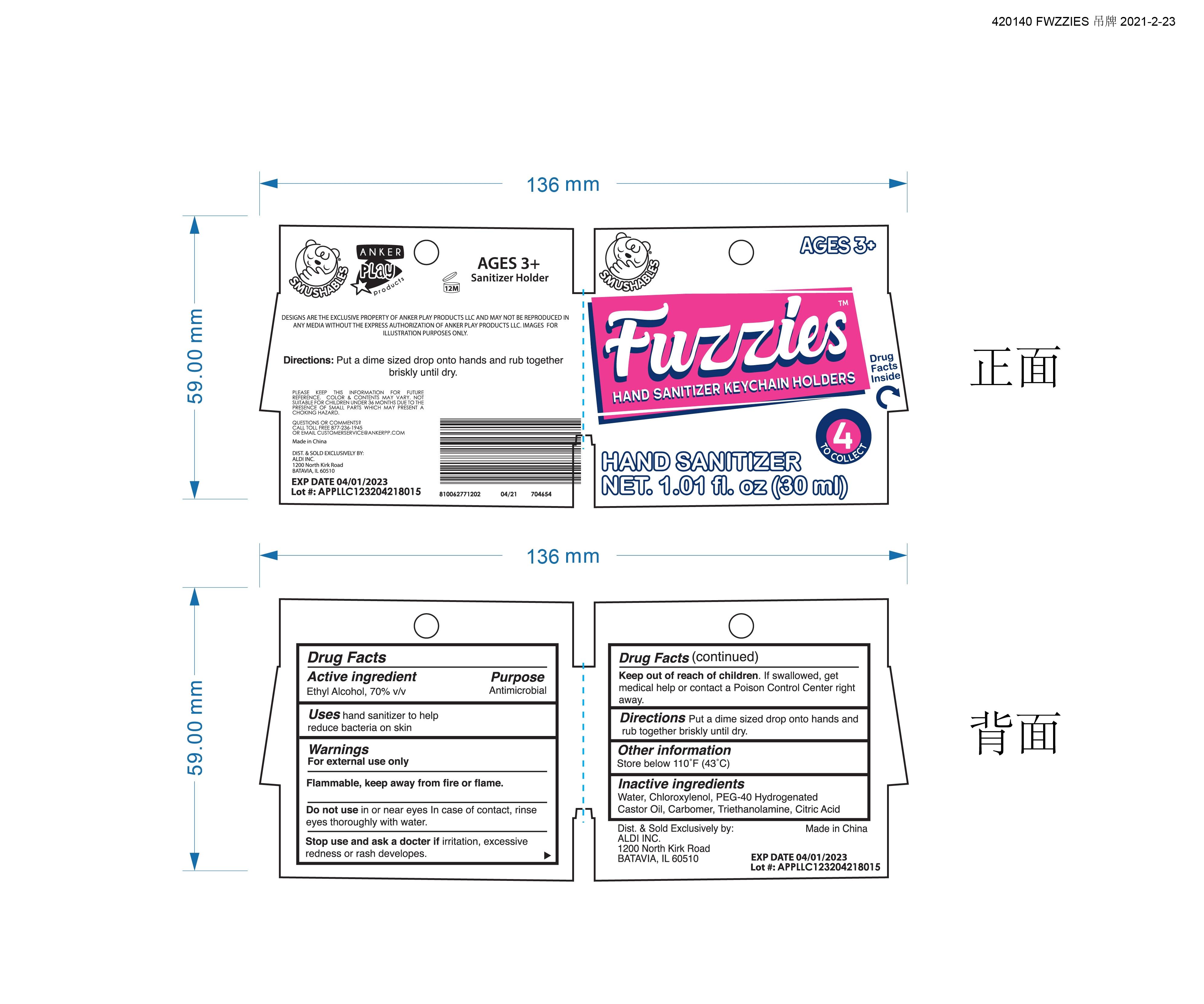 DRUG LABEL: Hand Sanitizer
NDC: 73946-005 | Form: GEL
Manufacturer: Yiwu Jiefei Daily Chemicals Co.,Ltd.
Category: otc | Type: HUMAN OTC DRUG LABEL
Date: 20210724

ACTIVE INGREDIENTS: ALCOHOL 70 mL/100 mL
INACTIVE INGREDIENTS: CASTOR OIL; PEG-40 HYDROGENATED LANOLIN; CITRIC ACID MONOHYDRATE; TROLAMINE; CHLOROXYLENOL; CARBOMER 934; WATER

73946-005 Hand Sanitizer Ethyl Alcohol 70%

Active Ingredient(s)

Ethyl Alcohol 70%

Purpose

Antimicrobial

Use

Uses hand sanitizer to help reduce bacteria on skin

Warnings

For external use only
Flammable, keep away from fire or flame.
Do not use in or near eyes ln case of contact, rinse
eyes thoroughly with water.
Stop use and ask a docter if irritation, excessive
redness or rash developes.

Keep out of reach of children. if swallowed, get medical help or
contact a Poison Control Center right away.

Directions

Put a dime sized drop onto hands and rub together briskly until dry.

Inactive ingredients

Water,Chloroxylenol, PEG-40 Hydrogenated
Castor Oil, Carbomer,Triethanolamine, Citric Acid